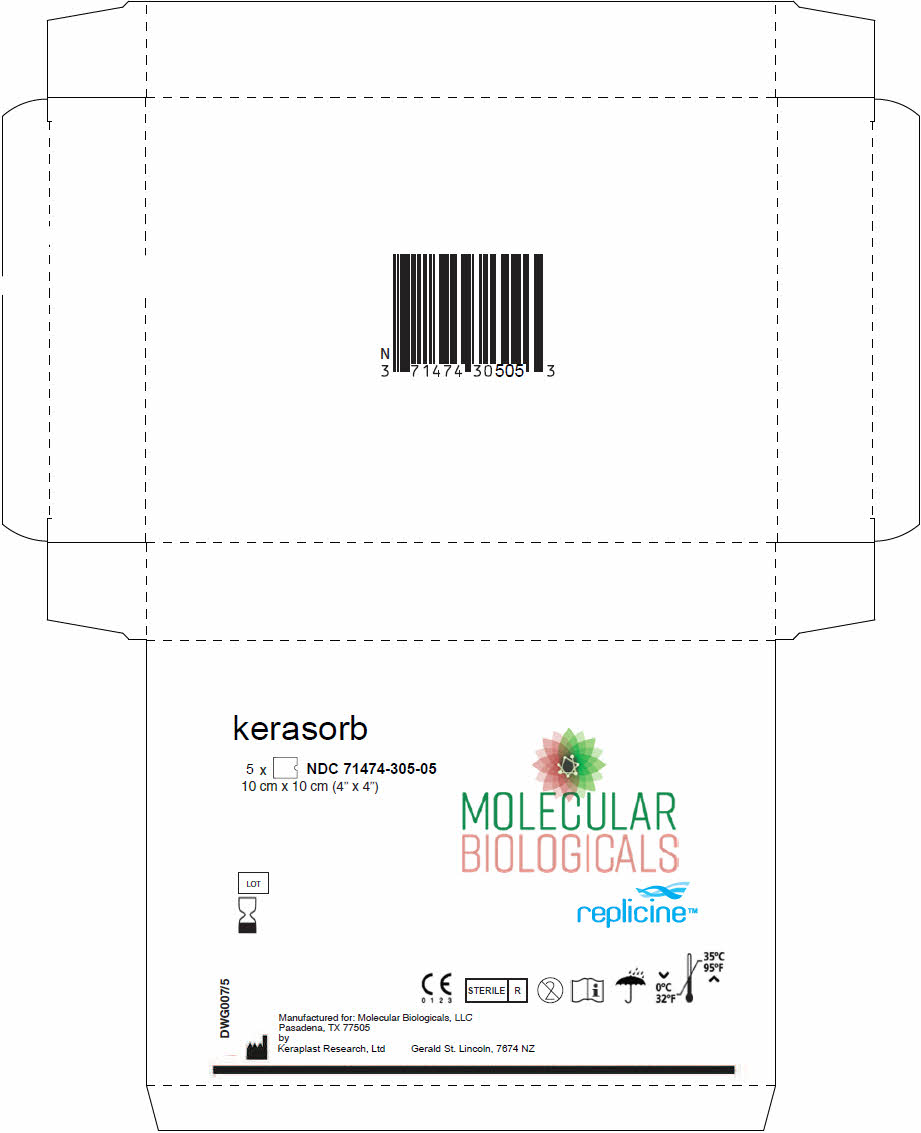 DRUG LABEL: kerasorb
NDC: 71474-305
Manufacturer: Molecular Biologicals, LLC
Category: other | Type: PRESCRIPTION MEDICAL DEVICE LABEL
Date: 20181219

ACTIVE INGREDIENTS: AMINO ACIDS, HAIR KERATIN 100 mg/1 1

Kerasorb®

Foam Wound Matrix

Rx Prescription Only - Single Use

STERILE | R

C E
0 1 2 3

CAUTION

Federal (U.S.A.) law restricts this device to sale by or on the order of a physician (or properly licensed Healthcare practitioner).

DESCRIPTION

Kerasorb® is an advanced bilayer wound care device designed for medium to highly exudative wounds. It is comprised of an absorbent foam with a Keratin (Replicine) wound matrix layer designed for wounds with medium to high exudate. Kerasorb foam wound matrix provides a scaffold for cellular migration, proliferation and capillary growth, while permitting drainage of excess fluids that may accumulate onto the wound bed. It is supplied in single use keratin foam matrix.

INDICATIONS FOR USE

Medium to High exudative wounds: Chronic wounds, surgical wounds, Donor sites/grafts, Diabetic ulcers, chronic ulcers of mixed vascular etiologies, venous stasis ulcers, Pressure ulcers (stages I-IV), partial & full thickness wounds, donor sites/grafts with medium to high exudate.

DOSAGE AND ADMINISTRATION

DIRECTIONS FOR USE (NOTE: ALWAYS HANDLE USING ASEPTIC TECHNIQUE)

WOUND BED PREPARATION & APPLICATION
1. Prepare wound area using standard debridement methods to ensure the wound is free of debris and devitalized tissue. The wound may be surgically debrided to ensure the wound edges contain viable tissue. A small influx of blood may be permitted into the wound.
2. Using sterile technique remove Kerasorb foam wound matrix from the pouch.
3. If necessary cut the Kerasorb foam wound matrix into a piece slightly larger than the outline of the wound area (approximately 1.5cm).
4. Apply Kerasorb® Foam Wound Matrix into the wound area. Ensure that the keratin matrix layer ("shiny side") makes contact with the wound bed. Secure in place using preferred method by healthcare provider(Steri-strips, sutures, tape). dressing.

5. After application use an appropriate occlusive
  MATRIX CHANGES & REAPPLICATIONS
6. Change kerasorb foam wound matrix as necessary. Frequency of dressing changes typically occur every 5-7 days, or as determined by the healthcare provider.
7. Once wound is cleansed using proper technique Kerasorb® Foam Wound Matrix may be reapplied.
8. Proceed with reapplication of appropriate occlusive secondary dressing.
9. If clinical signs of infection, excessive redness, blistering or suspected allergic reaction occurs the Matrix material should not be reapplied and proper notification and documentation should be done.

CONTRADICATIONS

Kerasorb® Foam Wound Matrix should not be used in patients with known sensitivity to keratin. The device is not indicated for third degree burns.

PRECAUTIONS

Do not reuse or re-sterilize. Do not use if package is open or if package is unsealed. Use prior to expiration date.

STORAGE

Do not use if package has been opened or damaged. Should be stored at a clean, dry location at ambient temperature.

HOW SUPPLIED

Kerasorb® is supplied sterile, in single use pouch containing one foam wound matrix.

Kerasorb® | 4cm × 4cm / unit | SKU/Model 71474-305-01
Kerasorb® | 4cm × 4cm / [Box of 5] units | SKU/Model 71474-305-05

Manufactured for:
Molecular Biologicals, LLC
Pasadena, TX 77505 | 1-844-793-9933
By Keraplast Research, Ltd
Gerald St. Lincoln, 7674 NZ

Kerasorb® is a registered trademark of Molecular Biologicals, LLC.
The product incorporates patented and /or patent pending technologies owned by Molecular Biologicals, LLC.

Issue Date 01Jan17
DWG005/9

PRINCIPAL DISPLAY PANEL - 5 Package Box

kerasorb

5 x NDC 71474-305-05
10 cm x 10 cm (4" x 4")

MOLECULAR
BIOLOGICALS
replicine™

LOT

DWG007/5

C E
0 1 2 3

STERILE R

i

⌄
0°C
32°F

35°C
95°F
⌃

Manufactured for: Molecular Biologicals, LLC
Pasadena, TX 77505
by
Keraplast Research, Ltd
Gerald St. Lincoln, 7674 NZ